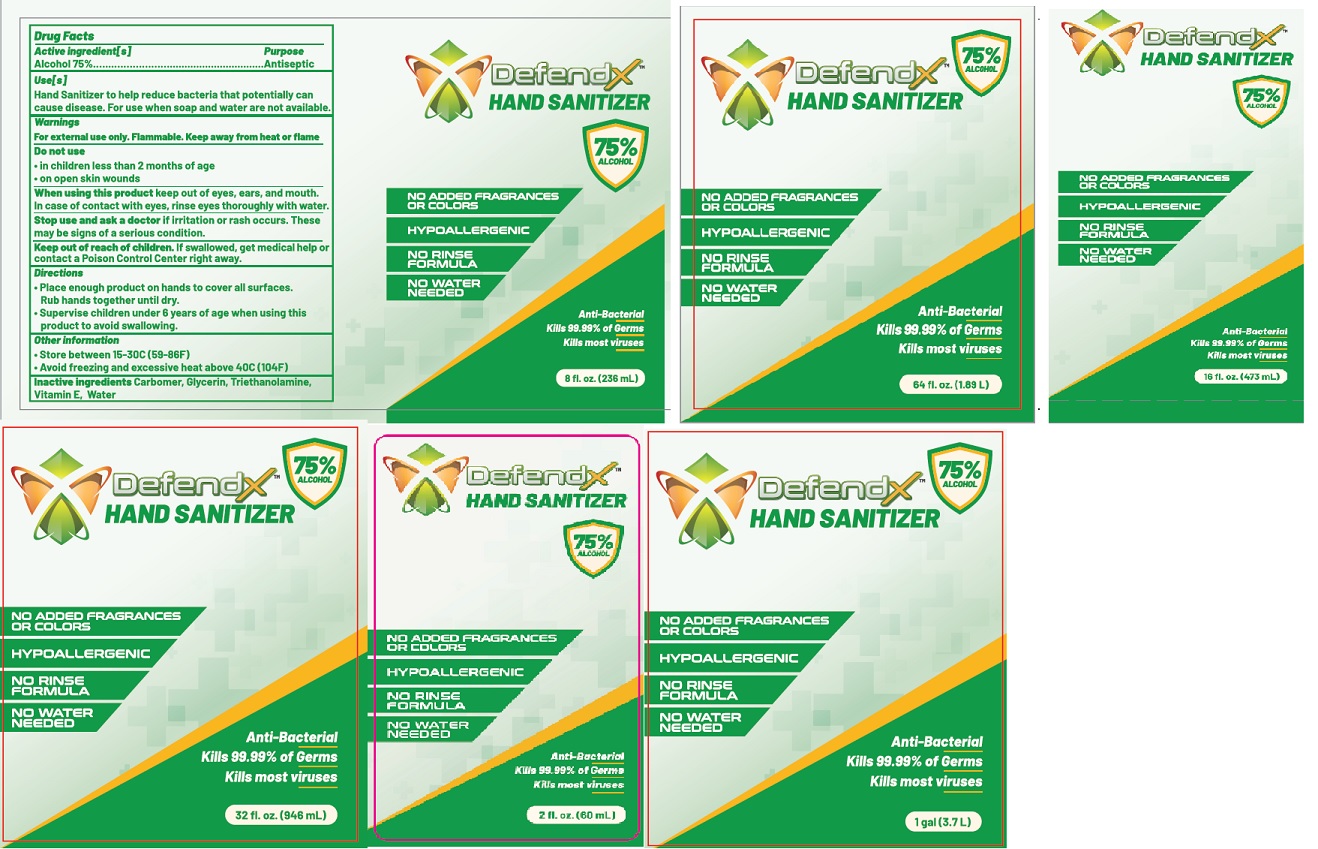 DRUG LABEL: DefendX Hand Sanitizer
NDC: 78256-003 | Form: GEL
Manufacturer: ETAILER LIMITED
Category: otc | Type: HUMAN OTC DRUG LABEL
Date: 20200611

ACTIVE INGREDIENTS: ALCOHOL 75 mL/100 mL
INACTIVE INGREDIENTS: GLYCERIN; WATER; TROLAMINE; .ALPHA.-TOCOPHEROL; CARBOMER HOMOPOLYMER, UNSPECIFIED TYPE

DefendX Hand Sanitizer Gel

Active Ingredient(s)

Alcohol 70% v/v.

Purpose

Antiseptic

Use

Hand Sanitizer to help reduce bacteria that potentially can cause disease. For use when soap and water are not available.

Warnings

For external use only. Flammable. Keep away from heat or flame

Do not use

- in children less than 2 months of age
- on open skin wounds

When using this product keep out of eyes, ears, and mouth. In case of contact with eyes, rinse eyes thoroughly with water.

Stop use and ask a doctor if irritation or rash occurs. These may be signs of a serious condition.

Keep out of reach of children. If swallowed, get medical help or contact a Poison Control Center right away.

Directions

- Place enough product on hands to cover all surfaces. Rub hands together until dry.
- Supervise children under 6 years of age when using this product to avoid swallowing.

Other information

- Store between 15-30C (59-86F)
- Avoid freezing and excessive heat above 40C (104F)

Inactive ingredients

Carbomer, Glycerin, Triethanolamine, Vitamin E, Water

Product Label (Principal Display Panel)

Distributed by:
DefendX
99 Wall Street #570
New York, NY 10005
United States of America
www.defendxonline.com
DefendX Hand Sanitizer (2 fl oz) NDC: 78256-003-02
DefendX Hand Sanitizer (8 fl oz) NDC: 78256-003-08
DefendX Hand Sanitizer (16 fl oz) NDC: 78256-003-16
DefendX Hand Sanitizer (32 fl oz) NDC: 78256-003-32
DefendX Hand Sanitizer (64 fl oz) NDC: 78256-003-64
DefendX Hand Sanitizer (1 Gal) NDC: 78256-003-01